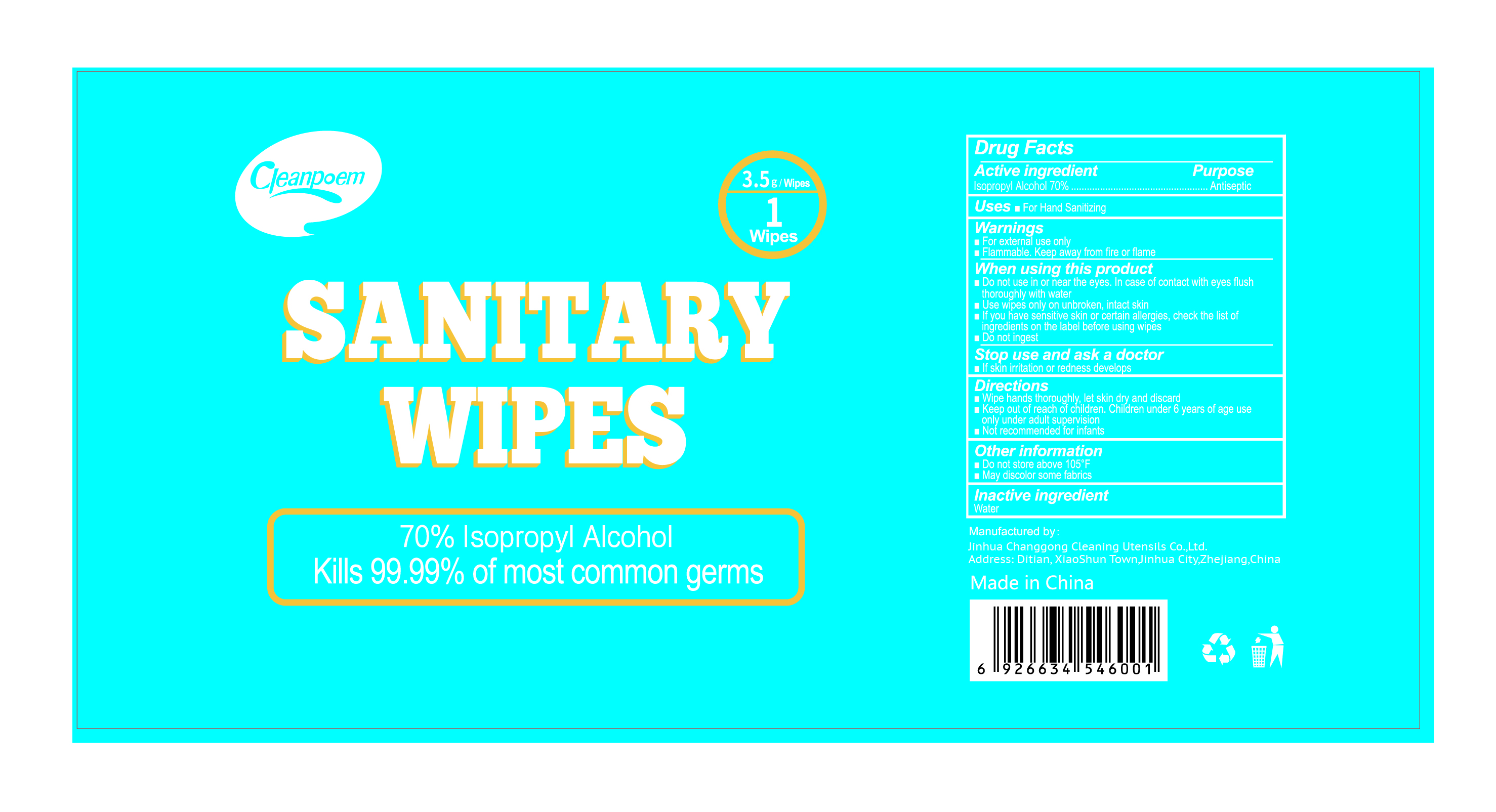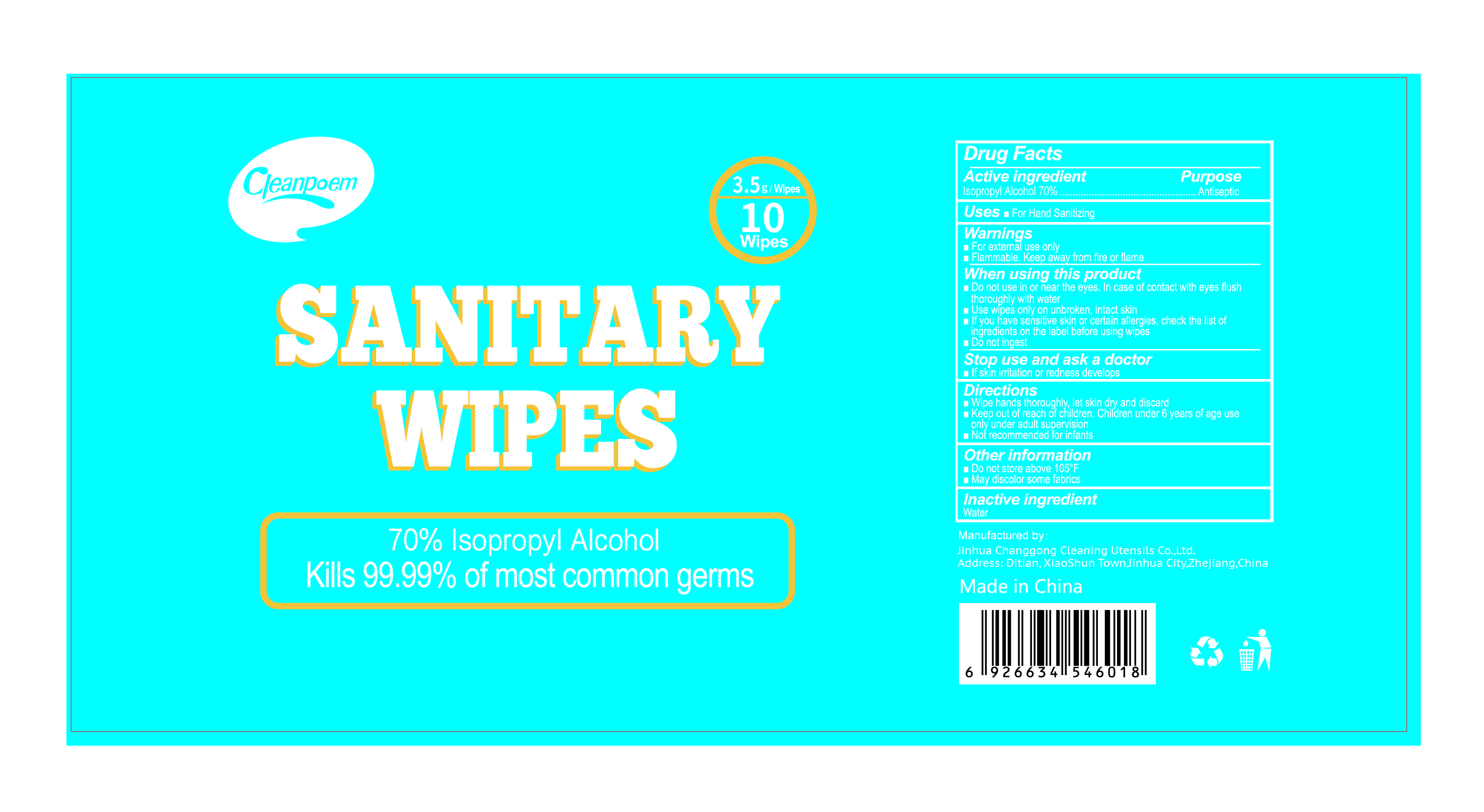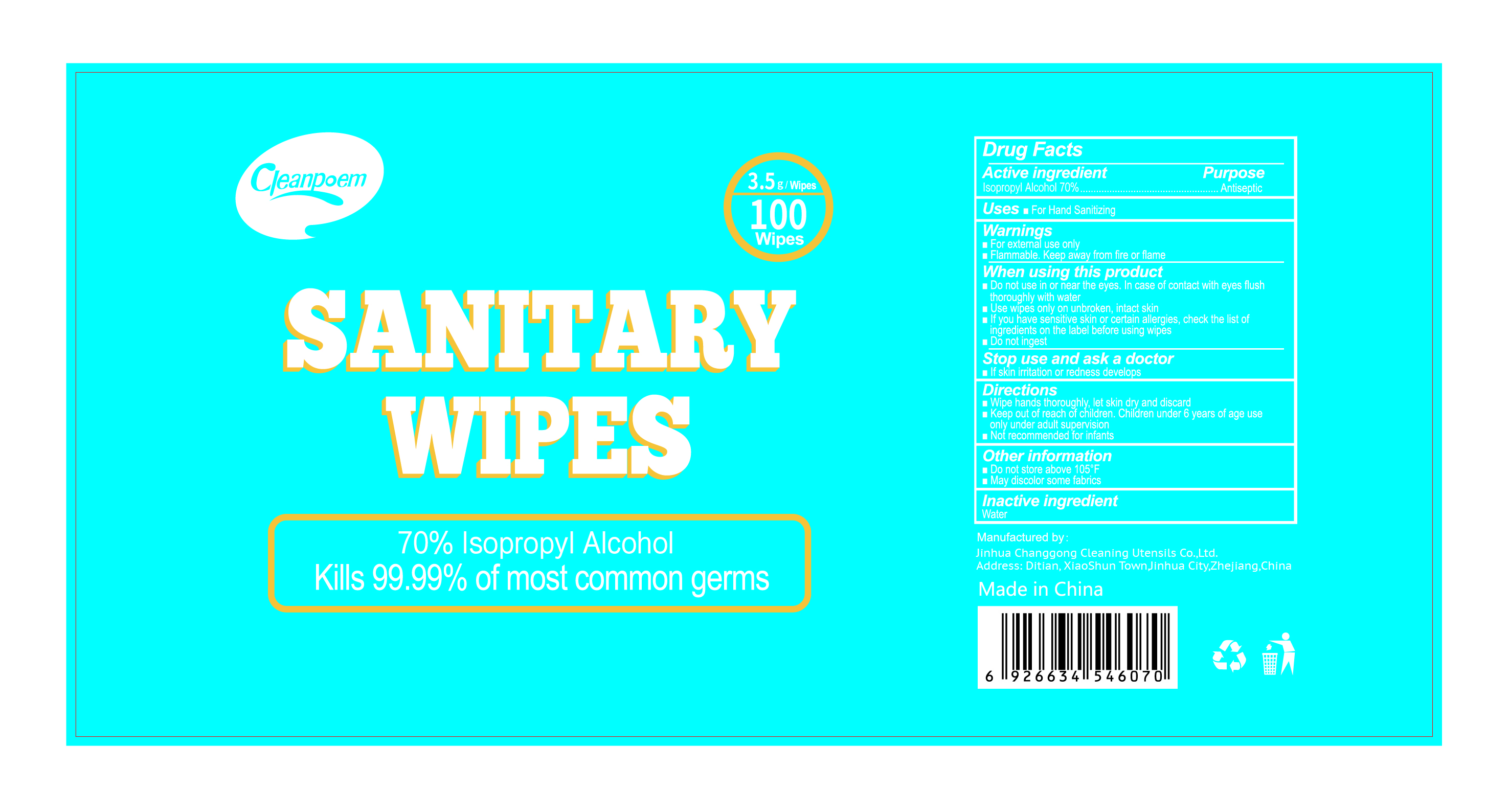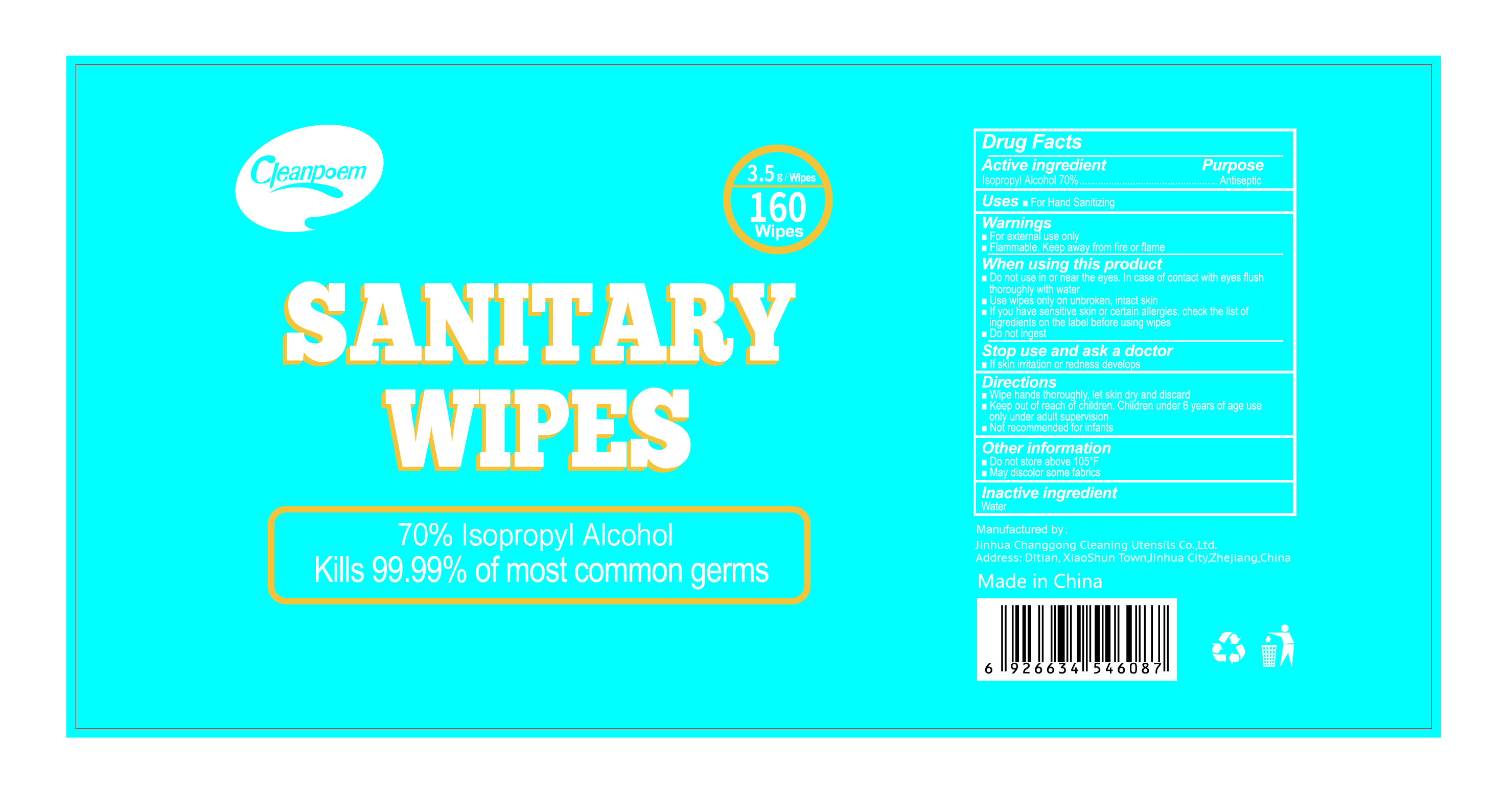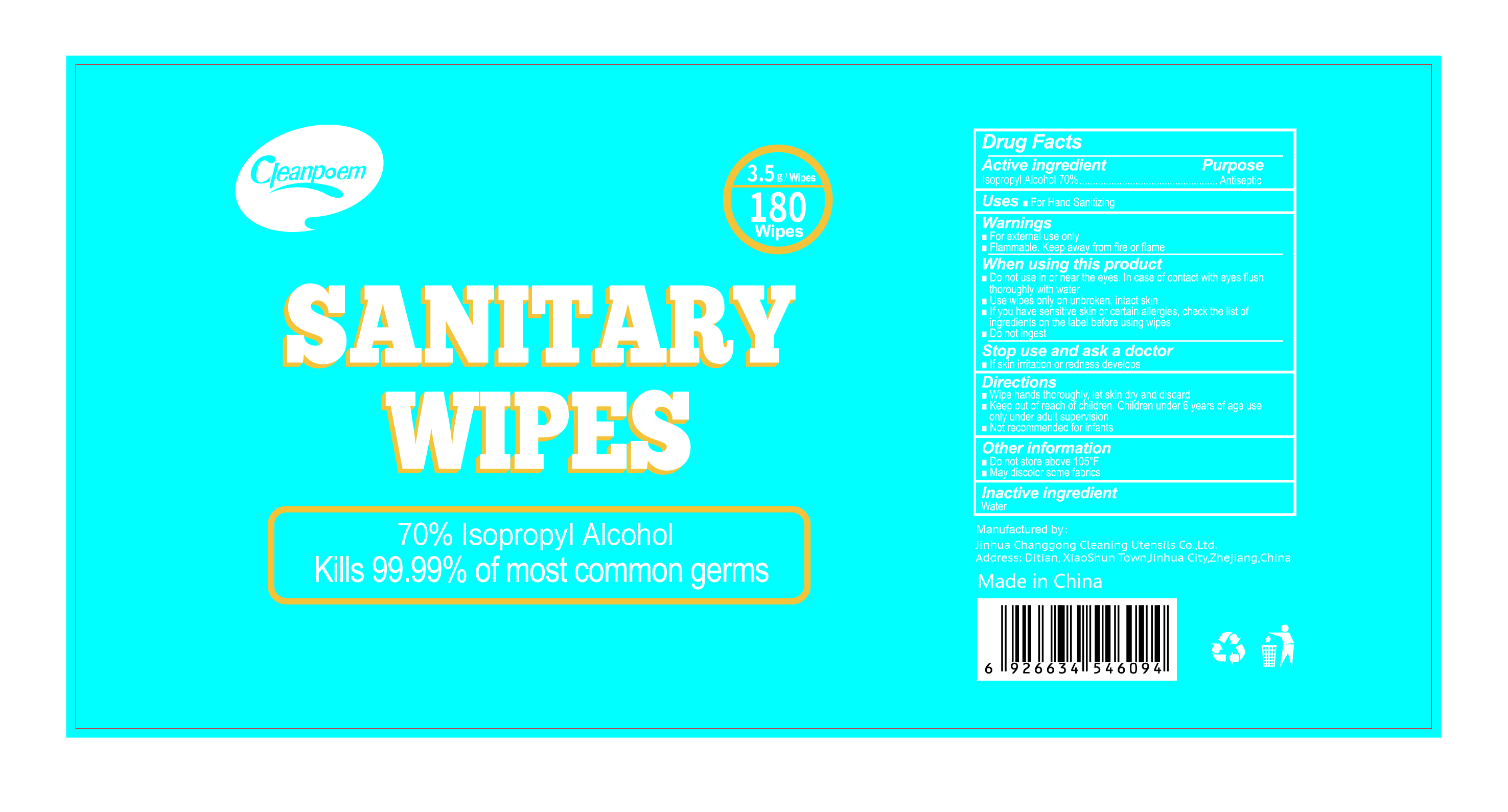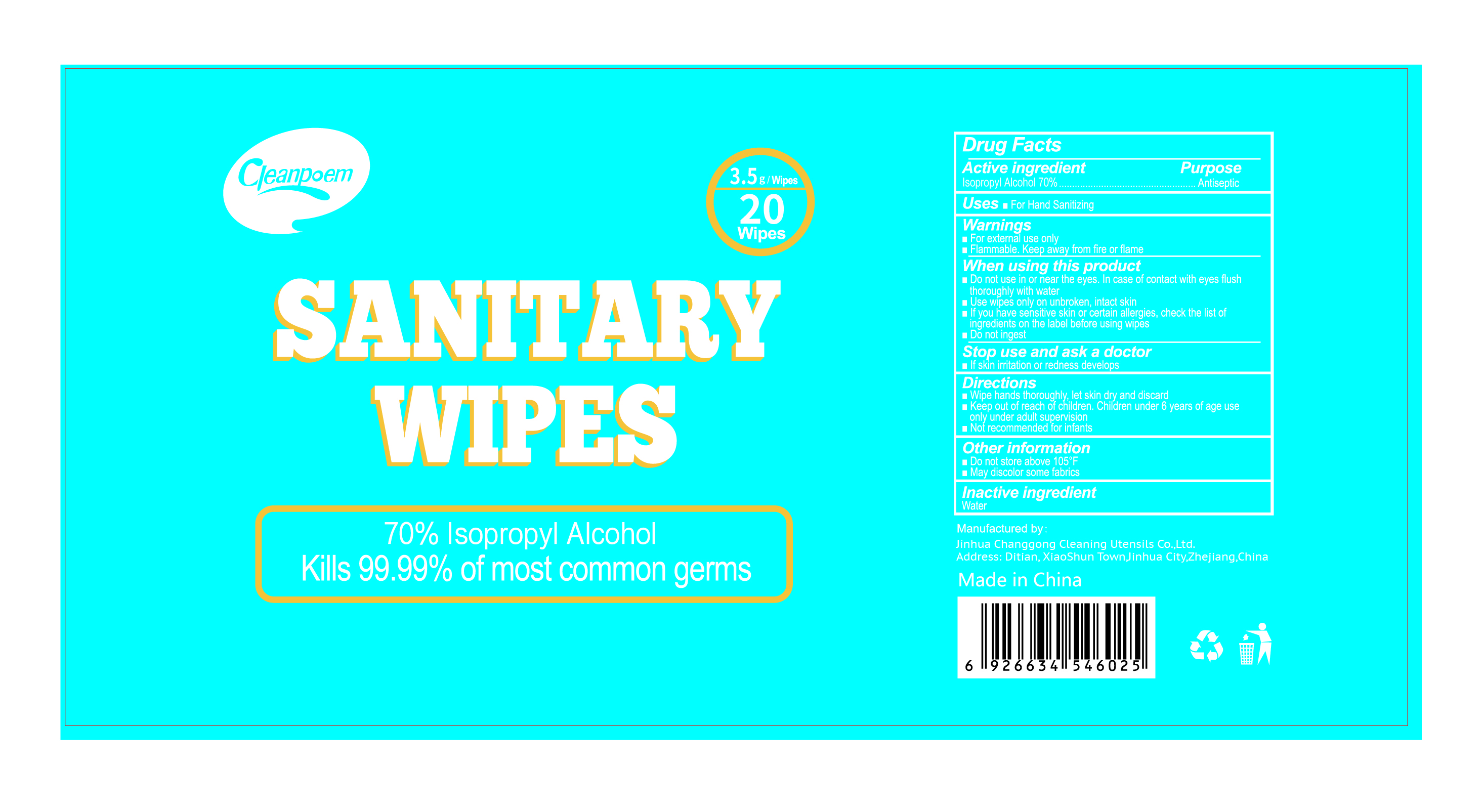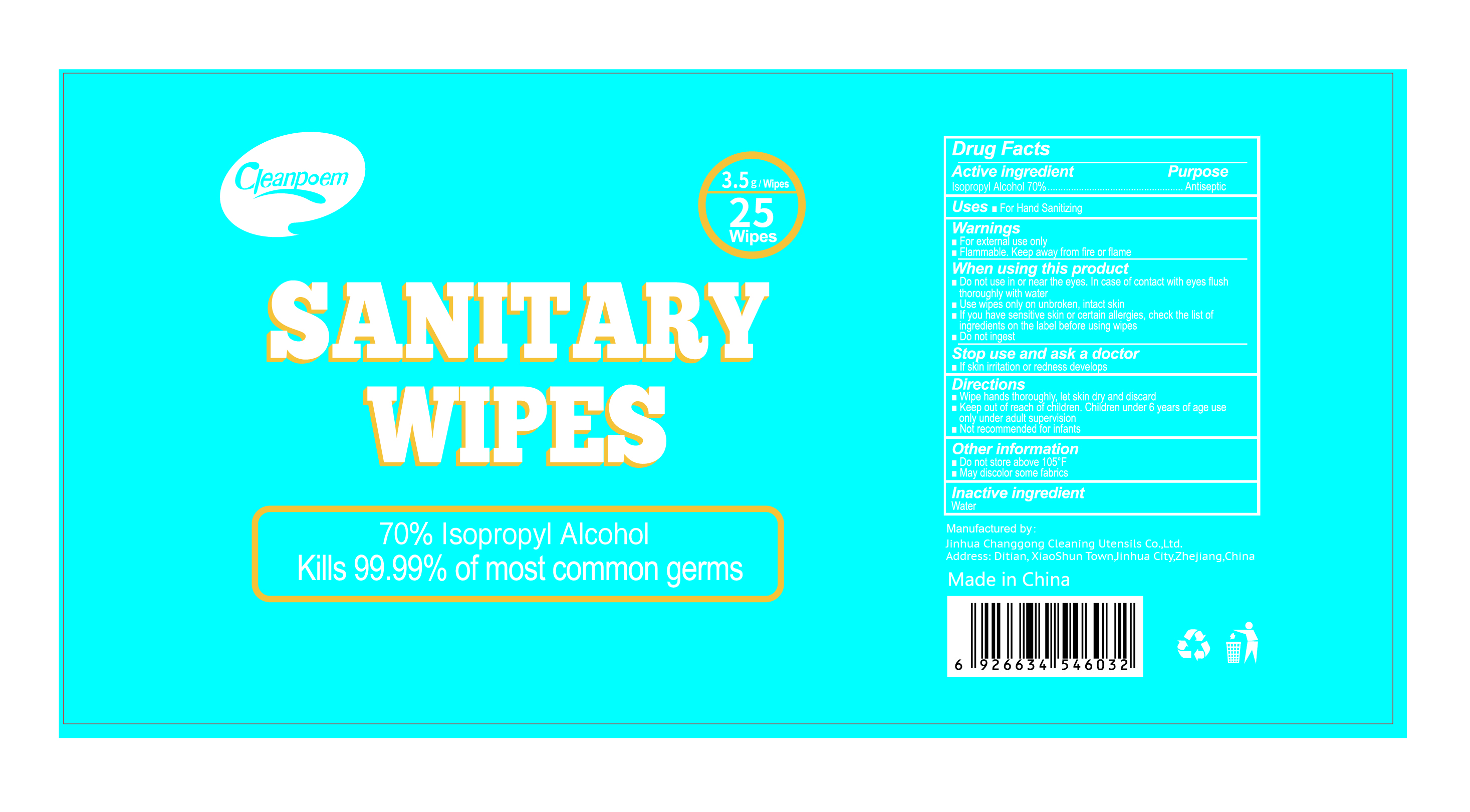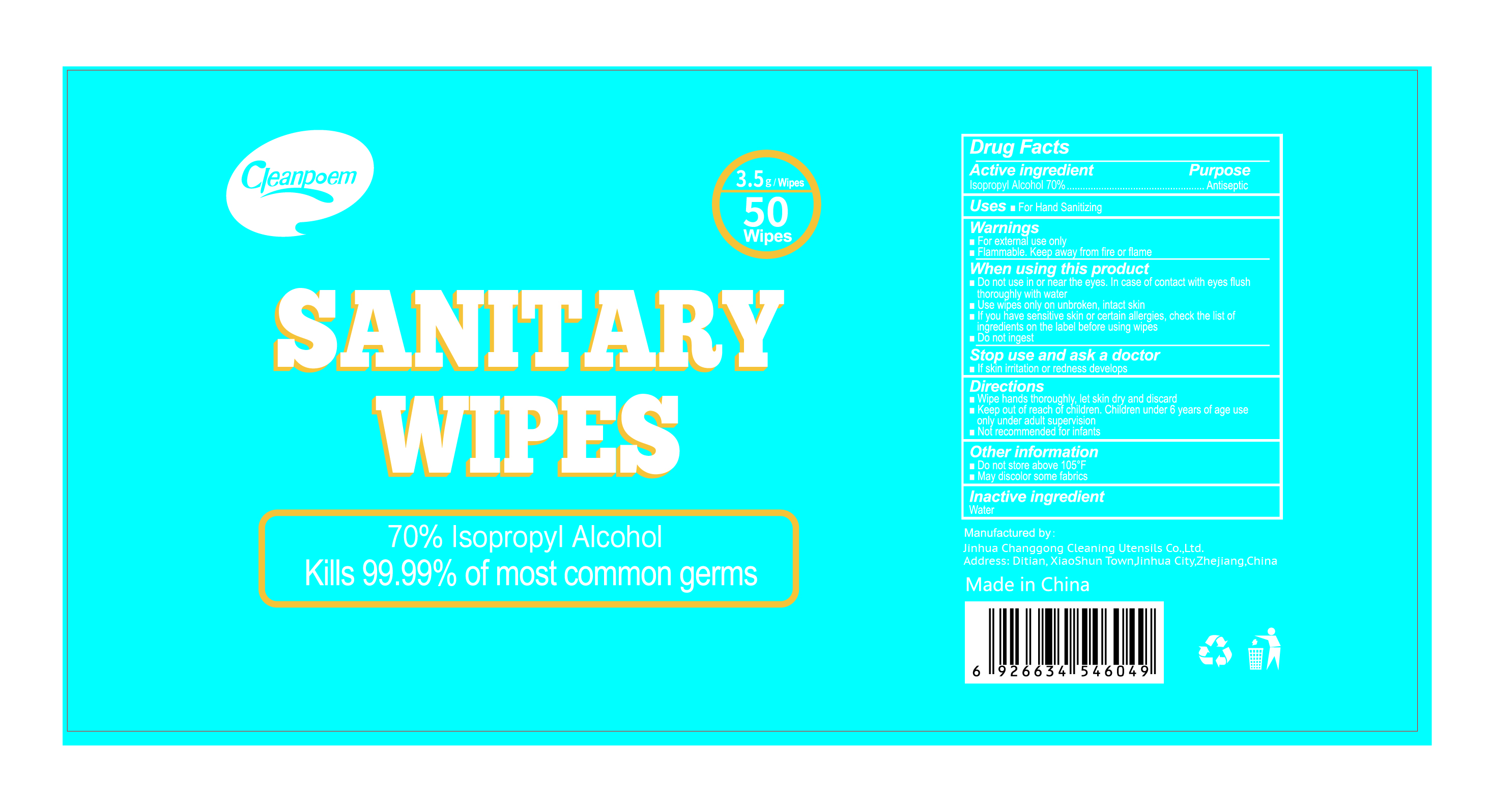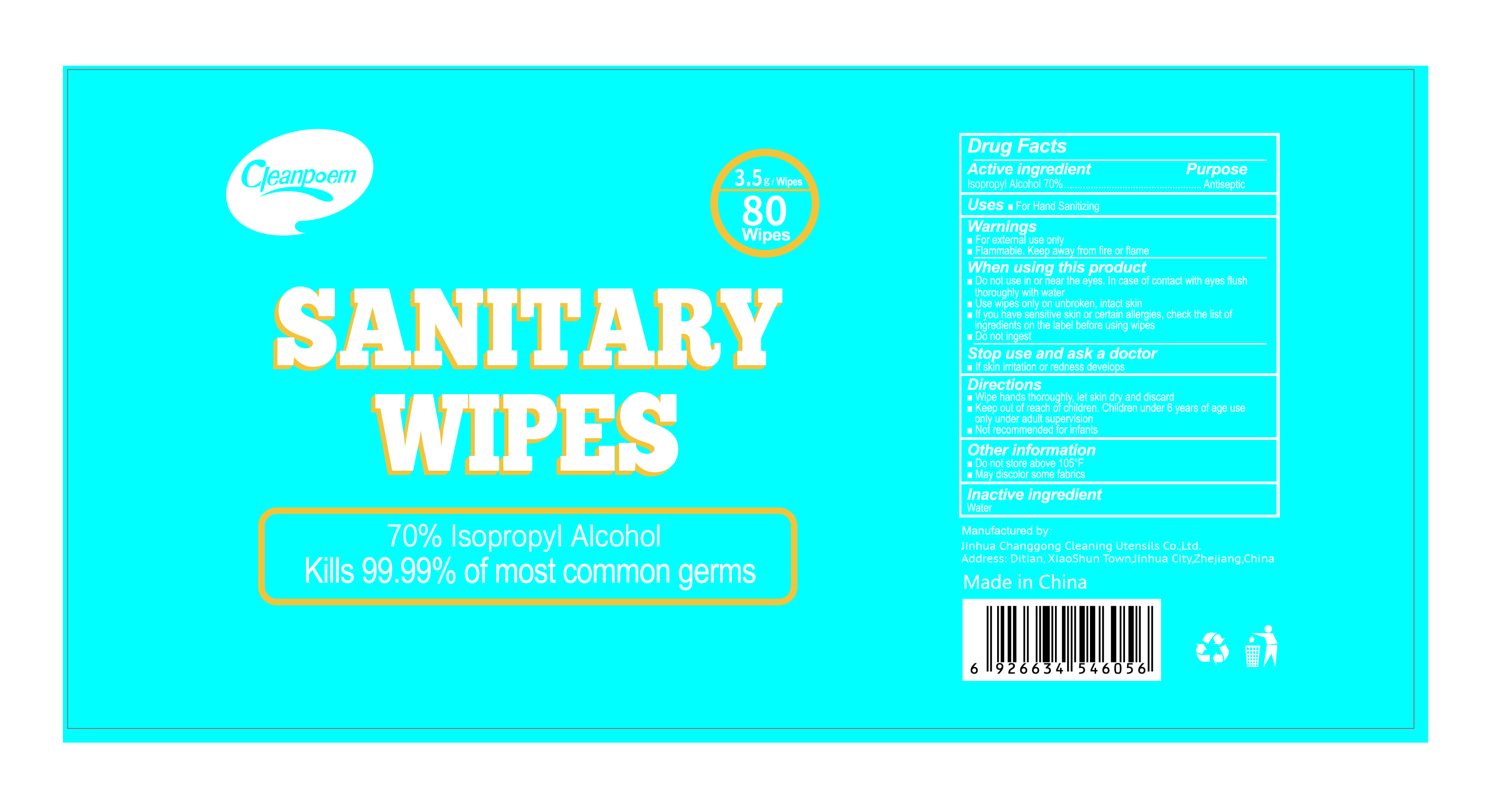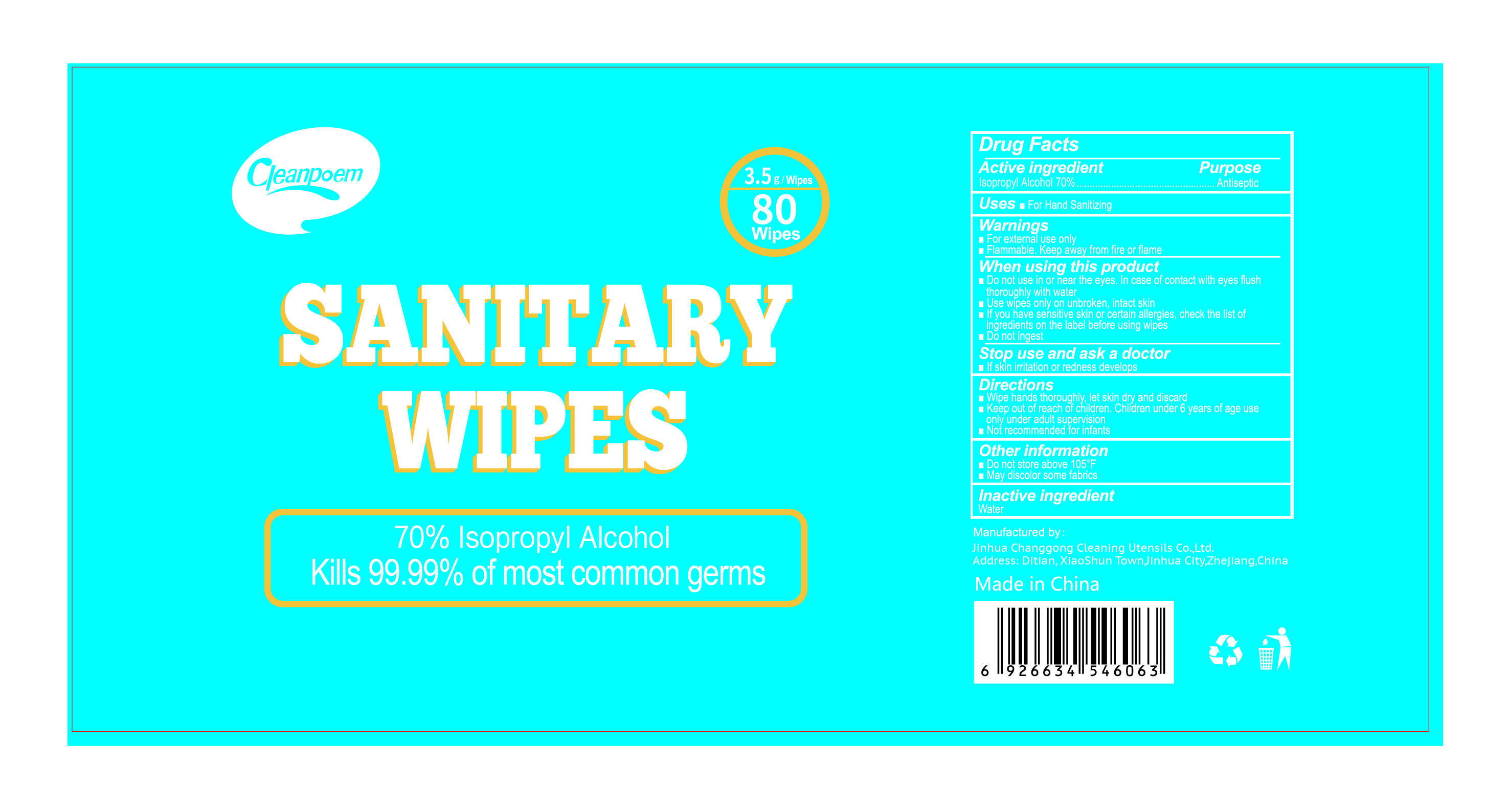 DRUG LABEL: SANITARY WIPES
NDC: 78505-003 | Form: CLOTH
Manufacturer: JINHUA CHANG GONG CLEANING UTENSILS CO.,LTD
Category: otc | Type: HUMAN OTC DRUG LABEL
Date: 20201226

ACTIVE INGREDIENTS: ISOPROPYL ALCOHOL 70 mL/100 1
INACTIVE INGREDIENTS: WATER

78505-003
SANITARY WIPES

Active ingredient

Isopropyl Alcohol 70%

Purpose

Antiseptic

Uses

For Hand Sanitizing

Warnings

For external use only
Flammable.Keep away from fire or flame

Do not use in or near the eyes.In case of contact with eyes flush thoroughly with water
Use wipes only on unbroken,intact skin
If you have sensitive skin or certain allergies,check the list of Ingredients on the label before using wipes
Do not ingest

When using this product

Do not use in or near the eyes.In case of contact with eyes flush thoroughly with water
Use wipes only on unbroken,intact skin
If you have sensitive skin or certain allergies,check the list of Ingredients on the label before using wipes
Do not ingest

Stop use and ask a doctor If skin irritation or redness develops

Stop use and ask a doctor If skin irritation or redness develops

Directions

Wipe hands thoroughly,let skin dry and discard
Keep out of reach of children.Children under 6 years of age use Only under adult supervision
Not recommended for infants

Other information

Do not store above 105°F

May discolor some fabrics

Inactive ingredient

Water

Package Label - Principal Display Panel

1 CLOTH IN 1 BAG; 78505-003-01

10 CLOTH IN 1 BAG; 78505-003-02

20 CLOTH IN 1 BAG; 78505-003-03

25 CLOTH IN 1 BAG; 78505-003-04

50 CLOTH IN 1 BAG; 78505-003-05

80 CLOTH IN 1 BAG; 78505-003-06

80 CLOTH IN 1 BOTTLE; 78505-003-07

100 CLOTH IN 1 BOTTLE; 78505-003-08

160 CLOTH IN 1 BOTTLE; 78505-003-09

180 CLOTH IN 1 BOTTLE; 78505-003-10